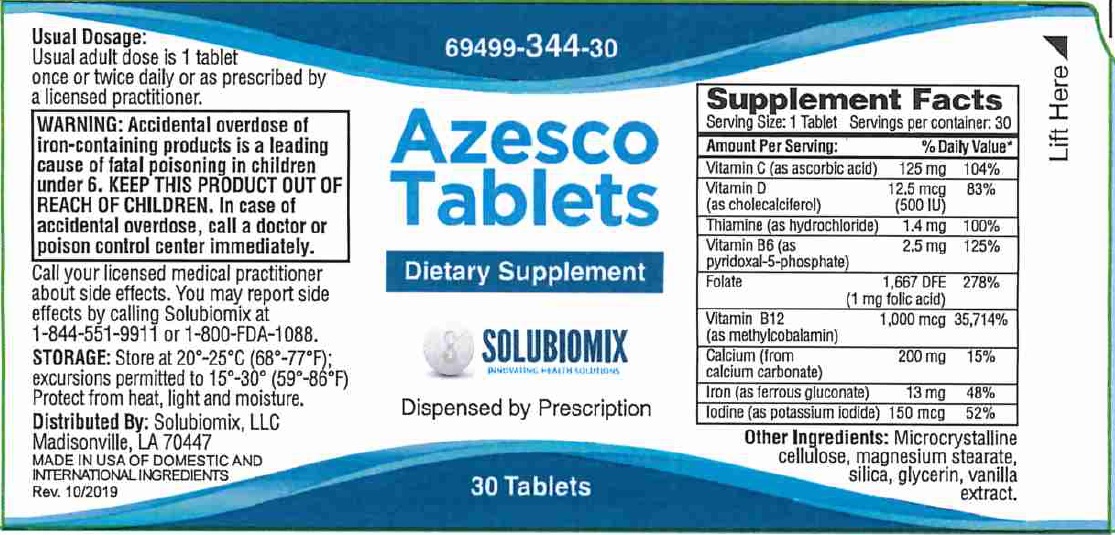 DRUG LABEL: Azesco
NDC: 69499-344 | Form: TABLET
Manufacturer: Solubiomix
Category: other | Type: DIETARY SUPPLEMENT
Date: 20251006

ACTIVE INGREDIENTS: ASCORBIC ACID 125 mg/1 1; cholecalciferol 0.0125 mg/1 1; THIAMINE 1.4 mg/1 1; PYRIDOXAL PHOSPHATE ANHYDROUS 2.5 mg/1 1; FOLIC ACID 1 mg/1 1; METHYLCOBALAMIN 1 mg/1 1; CALCIUM CARBONATE 200 mg/1 1; FERROUS GLUCONATE 13 mg/1 1; POTASSIUM IODIDE .15 mg/1 1
INACTIVE INGREDIENTS: CELLULOSE, MICROCRYSTALLINE; MAGNESIUM STEARATE; SILICON DIOXIDE

Azesco

HEALTH CLAIM:

Azezco Tablets - Prenatal/Postnatal/Folate Health Dietary Supplement

Dispensed by Prescription†

Supplement Facts
Serving Size: 1 Tablet
Servings per Bottle: 30
Amount Per Serving: | % Daily Value
Vitamin C (as ascorbic acid) | 125 mg | 104%
Vitamin D3 (as cholecalciferol) | 12.5 mcg | 83%
Thiamin (Vitamin B1 as thiamin HCl) | 1.4 mg | 100%
Vitamin B6 (as pyridoxal 5’ phosphate) | 2.5 mg | 125%
Folic Acid | 1 mg | 278%
Vitamin B12 (as methylcobalamin) | 1 mg | 3,5714%
Calcium (from calcium carbonate) | 200 mg | 15%
Iron (as ferrous gluconate) | 13 mg | 48%
Iodine (as potassium iodide) | 150 mcg | 52%

OTHER INGREDIENTS: cellulose, magnesium stearate, and silicon dioxide

DESCRIPTION:

Azesco Tablets is an orally administered prescription vitamin formulation for the clinical dietary management of suboptimal nutritional status
in patients where advanced folate supplementation is required and nutritional supplementation in physiologically stressful conditions for maintenance of good health is needed.

WARNING AND PRECAUTIONS

WARNING: Accidental overdose of iron-containing products is a leading cause of fatal poisoning in children under 6. KEEP THIS AND ALL DRUGS OUT OF THE REACH OF CHILDREN. In case of accidental overdose, call a doctor or poison control center immediately.

CONTRAINDICATIONSAzesco Tablets are contraindicated in patients with a known hypersensitivity to any of the ingredients. Do not take this product if you are presently taking mineral oil, unless directed by a doctor.

PRECAUTION
Folic acid alone is improper therapy in the treatment of pernicious anemia and other megaloblastic anemias where vitamin B is deficient. Folic acid in doses above 1 mg daily may obscure pernicious anemia in that hematologic remission can occur while neurological manifestations progress. Azesco Tablets should only be used under the direction and supervision of a licensed medical practitioner.

ADVERSE REACTIONS

Allergic sensitization has been reported following both oral and parenteral administration of folic acid. You may report side effects by calling 1-844-551-9911 or the FDA by calling 1-800-FDA-1088.

DOSAGE & ADMINISTRATION

Usual adult dose is 1 tablet taken orally once or twice daily or as prescribed by a licensed medical practitioner.

HOW SUPPLIED HEALTH CLAIM:

Azesco Tablets are available as tan, oblong tablets imprinted "0344" and are available in 30-count bottles (69499-344-30*). This product is not an Orange Book product.

Dispensed by Prescription†

MADE IN USA
Rev. 02/19

*Solubiomix does not represent these product codes to be National Drug Codes (NDC). Product codes are formatted according to standard industry practice, to meet the formatting requirement by pedigree reporting and supply-chain control including pharmacies.

† This product is a prescription-folate with or without other dietary ingredients that – due to increased folate levels increased risk associated with masking of B12 deficiency (pernicious anemia) requires administration under the care of a licensed medical practitioner (61 FR 8760).1-3 The most appropriate way to ensure pedigree reporting consistent with these regulatory guidelines and safety monitoring is to dispense this product only by prescription. This is not an Orange Book product. This product may be administered only under a physician’s supervision and all prescriptions using this product shall be pursuant to state statutes as applicable. The ingredients, indication or claims of this product are not to be construed to be drug claims.

1. Federal Register Notice of August 2, 1973 (38 FR 20750)
2. Federal Register Notice of October 17, 1980 (45 FR 69043, 69044)
3. Federal Register Notice of March 5, 1996 (61 FR 8760)

STORAGE AND HANDLING:

STORAGE: Store at 20°-25°C (68°-77°F); excursions permitted to 15°-30°C (59°-86°F) [See USP Controlled Room Temperature.] Protect from heat, light and moisture.

Tamper Evident: Do not use if seal is broken or missing.

Distributed by:
Solubiomix, LLC
Madisonville, LA 70447